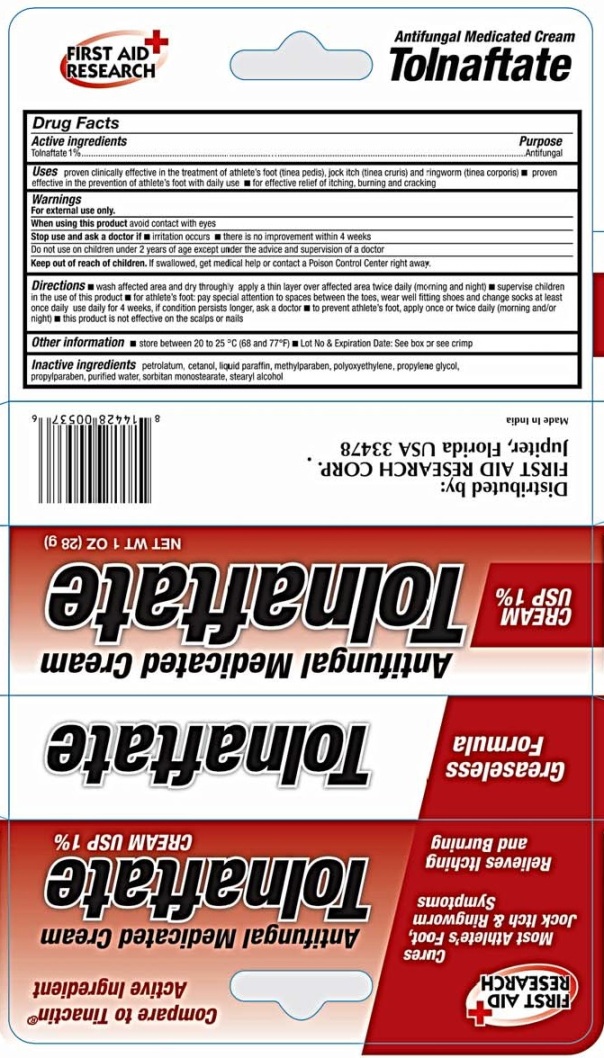 DRUG LABEL: First Aid Antifungal Medicated
NDC: 75983-002 | Form: CREAM
Manufacturer: First Aid Research Corp.
Category: otc | Type: HUMAN OTC DRUG LABEL
Date: 20220224

ACTIVE INGREDIENTS: TOLNAFTATE 10 mg/1 g
INACTIVE INGREDIENTS: PETROLATUM; CETYL ALCOHOL; MINERAL OIL; METHYLPARABEN; POLYETHYLENE GLYCOL, UNSPECIFIED; PROPYLENE GLYCOL; PROPYLPARABEN; WATER; SORBITAN MONOSTEARATE; STEARYL ALCOHOL

First Aid Antifungal Medicated Cream

Active ingredient

Tolnaftate 1%

Purpose

Antifungal

Uses

- proven clinically effective in the treatment of athlete's foot (tinea pedis), jock itch (tinea cruris) and ringworm (tinea corporis)
- proven effective in the prevention of athlete's foot with daily use
- for effective relief of itching, burning and cracking

Warnings

For external use only

When using this product avoid contact with the eyes

Stop use and ask a doctor if

- irritation occurs
- there is no improvement within 4 weeks

Do not use on children under 2 years of age except under the advice and supervision of a doctor.

Keep out of reach of children. If swallowed, get medical help or contact a Poison Control Center right away.

Directions

- wash affected area and dry thoroughly
- apply a thin layer over affected area twice daily (morning and night)
- supervise children in the use of this product
- for athlete's foot: pay special attention to spaces between the toes, wear well fitting shoes and change socks at least once daily
- use daily for 4 weeks, if condition persists longer, ask a doctor
- to prevent athlete's foot, apply once or twice daily (morning and/or night)
- this product is not effective on the scalps or nails

Other information

- store between 20 to 25°C (68 to 77°F)
- Lot No & Expiration Date: See box or see crimp

Inactive ingredients

petrolatum, cetanol, liquid paraffin, methylparaben, polyoxyethylene, propylene glycol, propylparaben, purified water, sorbitan monstearate, stearyl alchol.

Distributed by:

First Aid Research Corp.

Jupiter, Florida, USA 33478

Made in India

PRINCIPAL DISPLAY PANEL

First Aid Antifungal Medicated Cream
NET WT 1 OZ (28 g)